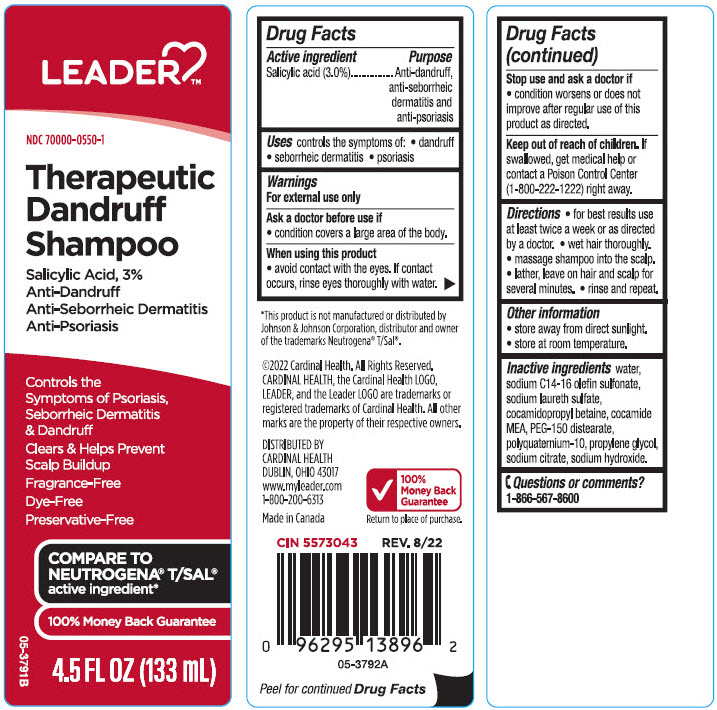 DRUG LABEL: Leader Therapeutic Dandruff
NDC: 70000-0550 | Form: SHAMPOO
Manufacturer: Cardinal Health, 110 dba LEADER
Category: otc | Type: HUMAN OTC DRUG LABEL
Date: 20240313

ACTIVE INGREDIENTS: Salicylic Acid 30 mg/1 mL
INACTIVE INGREDIENTS: Water; SODIUM LAURETH-3 SULFATE; Cocamidopropyl Betaine; COCO MONOETHANOLAMIDE; Sodium C14-16 Olefin Sulfonate; POLYQUATERNIUM-7 (70/30 ACRYLAMIDE/DADMAC; 1600000 MW); Propylene Glycol; PEG-150 Distearate; POLYQUATERNIUM-10 (30000 MPA.S AT 2%); SODIUM CITRATE, UNSPECIFIED FORM; Sodium Hydroxide

Leader™ Therapeutic Dandruff Shampoo
Anti-Dandruff, anti-seborrheic dematitis and anti-psoriasis

Drug Facts

Active ingredient

Salicylic Acid 3.0%

Purpose

Anti-dandruff, anti-seborrheic dermatitis and anti-psoriasis

Uses

control the symptoms of

- dandruff
- seborrheic dermatitis
- psoriasis

Warnings

For external use only

Ask a doctor before use if you have a condition which covers a large area of the body.

When using this product

- avoid contact with the eyes. If contact occurs, rinse eyes thoroughly with water.

Stop use and ask a doctor if

- condition worsens or does not improve after regular use of this product as directed.

Keep out of reach of children. If swallowed, get medical help or contact a Poison Control Center (1-800-222-1222) right away.

Directions

- for best results use at least twice a week or as directed by a doctor
- wet hair thoroughly
- massage shampoo into scalp
- lather, leave on hair and scalp for several minutes
- rinse and repeat.

Other information

- store at room temperature
- store away from direct sunlight.

Inactive ingredients

water, sodium C14-16 olefin sulfonate, sodium laureth sulfate, cocamidopropyl betaine, cocamide MEA, PEG-150 distearate, polyquaternium-10, propylene glycol, sodium citrate, sodium hydroxide.

Questions or comments?

1-866-567-8600

DISTRIBUTED BY
CARDINAL HEALTH
DUBLIN, OHIO 43017

PRINCIPAL DISPLAY PANEL - 133 mL Bottle Label

LEADER™

NDC 70000-0550-1

Therapeutic
Dandruff
Shampoo

Salicylic Acid, 3%
Anti-Dandruff
Anti-Seborrheic Dermatitis
Anti-Psoriasis

Controls the
Symptoms of Psoriasis,
Seborrheic Dermatitis
& Dandruff
Clears & Helps Prevent
Scalp Buildup
Fragrance-Free
Dye-Free
Preservative-Free

COMPARE TO
NEUTROGENA® T/SAL®
active ingredient*

100% Money Back Guarantee

4.5 FL OZ (133 mL)

05-3791B